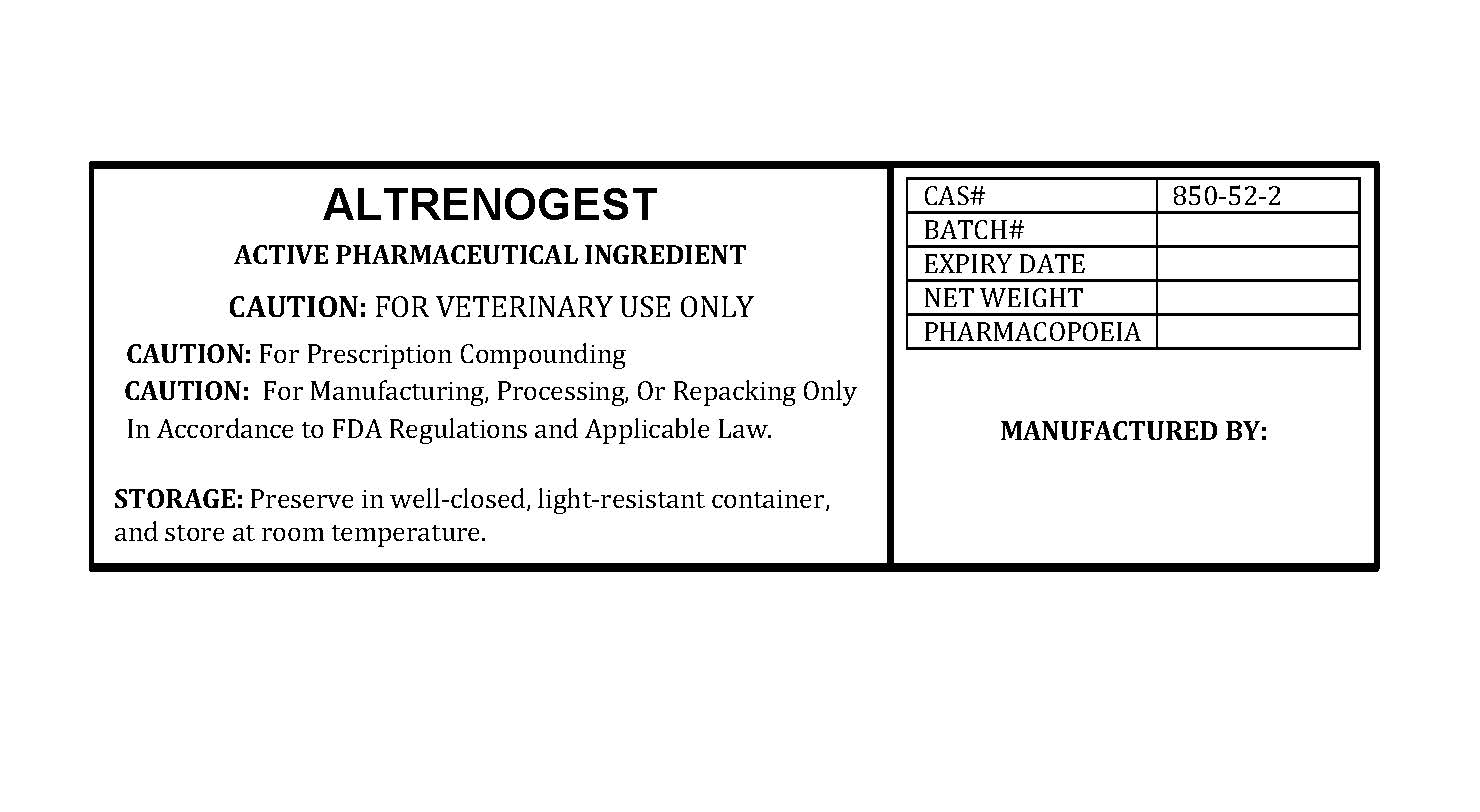 DRUG LABEL: ALTRENOGEST
NDC: 86184-003 | Form: POWDER
Manufacturer: MAEDA INC
Category: other | Type: BULK INGREDIENT - ANIMAL DRUG
Date: 20251025

ACTIVE INGREDIENTS: ALTRENOGEST 1 g/1 g

ALTRENOGEST

PACKAGE LABEL

altrenogestlabelfile.jpg